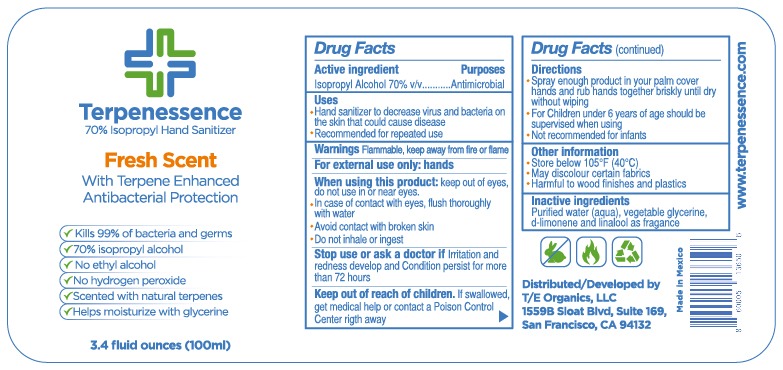 DRUG LABEL: SANITIZER
NDC: 80535-0003 | Form: LIQUID
Manufacturer: FARMACIA SAN ARCANGEL, S.A DE C.V
Category: otc | Type: HUMAN OTC DRUG LABEL
Date: 20201019

ACTIVE INGREDIENTS: ISOPROPYL ALCOHOL 70 mL/100 mL
INACTIVE INGREDIENTS: LIMONENE, (+)-; WATER; LINALOOL, (+/-)-; GLYCERIN

Active Ingredient

Isopropyl Alcohol 70% v/v

Purposes

Antimicrobial

Uses

Hand sanitizer to decrease virus and bacteria on the skin that could cause disease

Recommended for repetead use

Warnings

Flammable, keep away form fire or flame

For external use only: hands

When using this product

keep out of eyes, do not use in or near eyes.

In case of contact with eyes, flush thorougly with water

avoid contact with broken skin

do not inhale or ingest

Stop use or ask a doctor if

Irritation and redness develop and condition persist for more than 72 hours

Keep out of reach of children

If swallowed, get medical help or contact a poison control center right away

Directions

Put enough product in your palm cover hands and rub hands together briskly until dry without wiping

for children under 6 years of age should be supervised when using

Other information

Store below 105F (40C)

may discolour certain fabrics

harmful to wood finishes and plastics

Inactive ingredients

Purified water (aqua), vegetable glycerine, d-limonene and linalool as fragance

Principal Display

70% Isopropyl hand sanitizer

Fresh scent

with terpene enhaced

antibacterial protection

kills 99% of bacteria and germs

70% isopropyl alcohol

no ethyl alcohol

no hudrogen peroxide

scented with natural terpenes

helps moisturize with glycerine

3.4 fluid onces (100 ml)